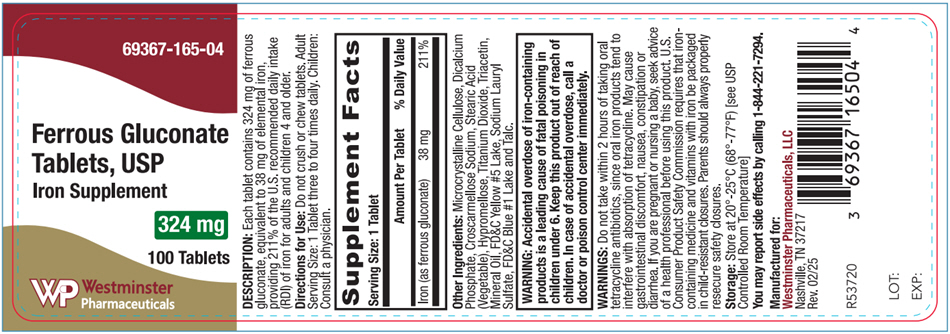 DRUG LABEL: Ferrous Gluconate
NDC: 69367-165 | Form: TABLET
Manufacturer: Westminster Pharmaceuticals, LLC
Category: other | Type: DIETARY SUPPLEMENT
Date: 20250710

ACTIVE INGREDIENTS: FERROUS GLUCONATE 38 mg/1 1
INACTIVE INGREDIENTS: CROSCARMELLOSE SODIUM; HYPROMELLOSE, UNSPECIFIED; TITANIUM DIOXIDE; FD&C BLUE NO. 1 ALUMINUM LAKE; TRIACETIN; MINERAL OIL; FD&C YELLOW NO. 5 ALUMINUM LAKE; SODIUM LAURYL SULFATE; TALC

Ferrous Gluconate

DESCRIPTION

Each tablet contains 324 mg of ferrous gluconate, equivalent to 38 mg of elemental iron, providing 211% of the U.S. recommended daily intake (RDI) of iron for adults and children 4 and older.

Directions for Use

Do not crush or chew tablets. Adult Serving Size: 1 tablet three to four times daily. Children: Consult a physician.

STATEMENT OF IDENTITY

Supplement Facts
Serving Size 1 Tablet
 | Amount Per Tablet | % Daily Value [Percent Daily Value (DV) are based on a 2000 calorie diet. Your daily value may be higher or lower depending on your calorie intake.]
Iron (as ferrous gluconate) | 38 mg | 211%

Other Ingredients: Microcrystalline Cellulose, Dicalcium Phosphate Dihydrated, Croscarmellose Sodium, Stearic Acid (Vegetable), Silicon Dioxide, Magnesium Stearate (Vegetable), Sodium Starch Glycolate, Hypromellose, Polyethylene Glycol, FD&C Yellow #6, FD&C Blue #1, Titanium Dioxide.

WARNINGS

WARNING: Accidental overdose of iron-containing products is a leading cause of fatal poisoning in children under 6. Keep this product out of reach of children. In case of accidental overdose, call a doctor or poison control center immediately.

WARNINGS

Do not take within 2 hours of taking oral tetracycline antibiotics, since oral iron products tend to interfere with absorption of tetracycline. May cause gastrointestinal discomfort, nausea, constipation or diarrhea. If you are pregnant or nursing a baby, seek advice of a health professional before using this product. U.S. Consumer Product Safety Commission requires that iron-containing medicine and vitamins with iron be packaged in child-resistant closures. Parents should always properly resecure safety closures.

Storage

Store at 20° - 25°C (68° - 77°F)[see USP Controlled Room Temperature]

You may report side effects by calling 1-844-221-7294.

HEALTH CLAIM

Manufactured for:
Westminster Pharmaceuticals, LLC
Nashville, TN 37217
Rev. 05/22

PRINCIPAL DISPLAY PANEL - 324 mg Tablet Bottle Label

69367-165-04

Ferrous Gluconate
Tablets, USP
Iron Supplement

324 mg

100 Tablets

Westminster
Pharmaceuticals